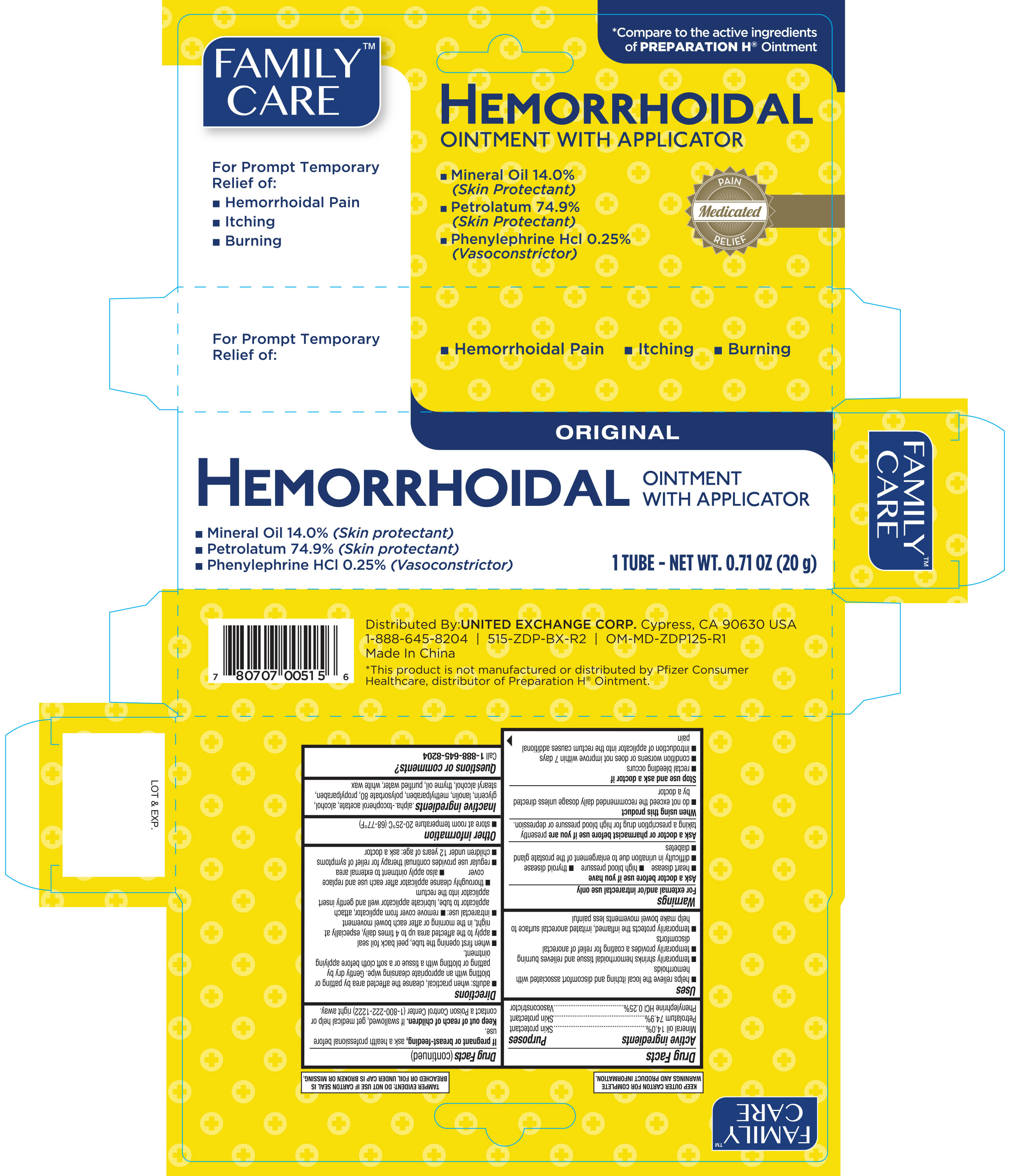 DRUG LABEL: Family Care Hemorrhoidal
NDC: 65923-003 | Form: OINTMENT
Manufacturer: United Exchange Corp
Category: otc | Type: HUMAN OTC DRUG LABEL
Date: 20251022

ACTIVE INGREDIENTS: MINERAL OIL 140 mg/100 g; PETROLATUM 749 mg/100 g; PHENYLEPHRINE HYDROCHLORIDE 2.5 mg/100 g
INACTIVE INGREDIENTS: GLYCERIN; LANOLIN; METHYLPARABEN; PROPYLPARABEN; STEARYL ALCOHOL; THYME OIL; ALPHA-TOCOPHEROL ACETATE; WATER; WHITE WAX; ALCOHOL; POLYSORBATE 80

Family Care Hemorrhoidal Ointment 0.67oz (with applicator) 515

Active ingredients Purpose

Mineral oil 14%.........................................................Protectant

Petrolatum 74.9%.....................................................Protectant

Phenylephrine HCl 0.25%...................................Vasoconstrictor

Uses

- helps relieve the local itching and discomfort associated with hemorrhoids
- temporarily shrinks hemorrhoidal tissue and relieve burning
- temporarily provides a coating for relief of anorectal discomforts
- temporarily protects the inflamed, irritated anorectal surface to help make bowel movements less painful

WARNINGS

Warnings For external use only / or intrarectal use only

Ask a doctor before use if you have

- heart disease
- high blood pressure
- thyroid disease
- difficulty in urination due to enlargement of the prostate gland
- diabetes

Ask a doctor or a pharmacist before use if you are now taking a prescription drug for high blood pressure or depression

When using this product do not use more than the recommended daily dosage unless directed by a doctor

Stop use and ask a doctor if

- rectal bleeding occurs
- condition gets worse or does not get better within 7 days
- introduction of applicator into the rectum causes additional pain

PREGNANCY OR BREAST FEEDING

If pregnant or breast-feeding, ask a physician before use.

Keep out of reach of children. If swallowed, get medical help or contact a Poison Control Center right away.

Directions

- adults: when practical, cleanse the affected area by patting or blotting with an appropriate cleansing wipe. Gently dry by patting or blotting with a tissue or a soft cloth before applying ointment
- when first opening tube, peel back foil seal
- apply to the affected area up to 4 times daily, especially at night, in the morning or after each bowel movement
- intrarectal use: remove cover from applicator, attach applicator to tube, lubricate applicator well and gently insert applicator into the rectum
- thoroughly cleanse applicator after each use and replace cover
- also apply ointment to external area
- regular use provides continual therapy for relief of symptoms
- children under 12 years of age: ask a doctor

Other information

- store at 20° C to 25°C (68° to 77°F)

Inactive ingredients

.alpha.-tocopherol acetate, alcohol, glycerin, lanolin, methylparaben, polysorbate 80, propylparaben, stearyl alcohol, thyme oil, purified water, white wax

DOSAGE AND ADMINISTRATION

Distributed by:

United Exchange Corp

Cypress, CA 90630 USA

Made in China